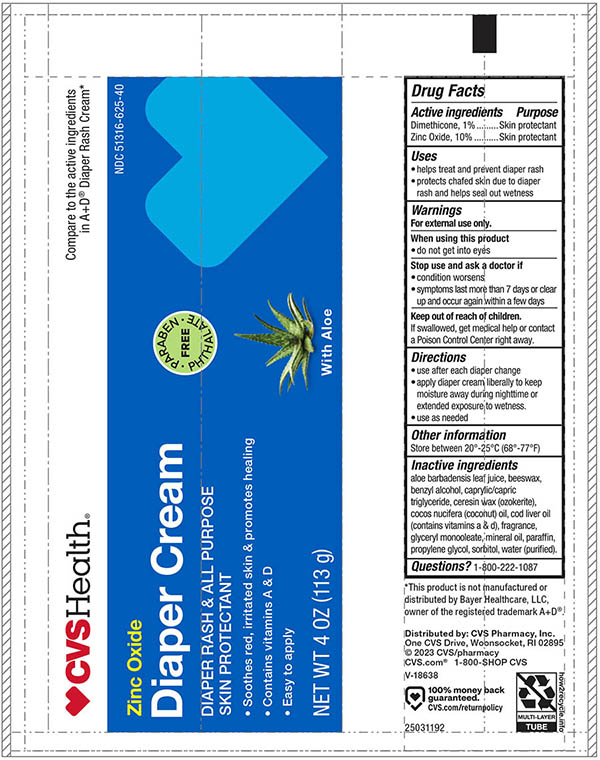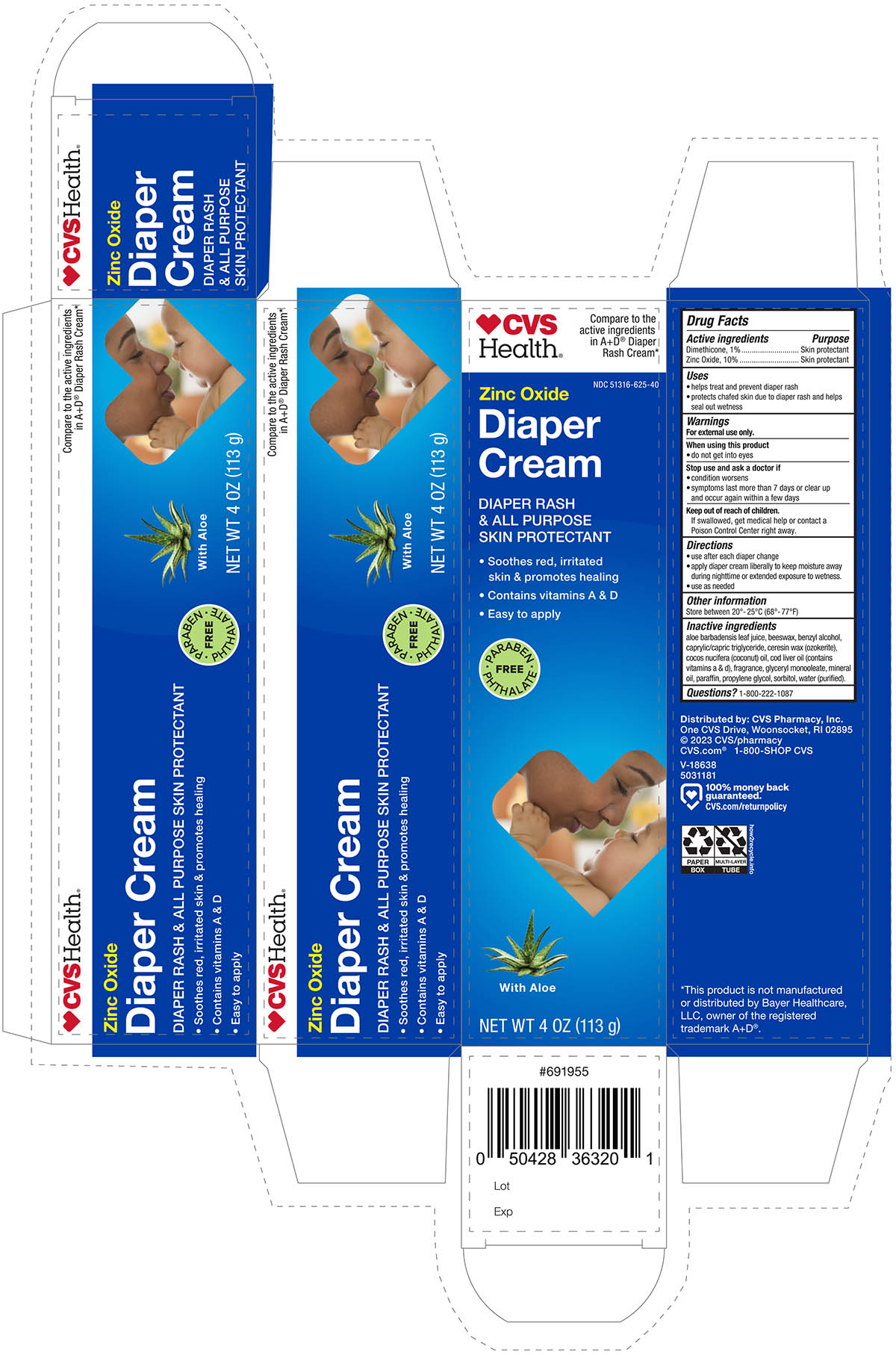 DRUG LABEL: CVS Diaper Rash
NDC: 51316-625 | Form: OINTMENT
Manufacturer: CVS Health
Category: otc | Type: HUMAN OTC DRUG LABEL
Date: 20241112

ACTIVE INGREDIENTS: ZINC OXIDE 100 mg/1 g; DIMETHICONE 10 mg/1 g
INACTIVE INGREDIENTS: ALOE VERA LEAF; SYNTHETIC BEESWAX; BENZYL ALCOHOL; MEDIUM-CHAIN TRIGLYCERIDES; CERESIN; COCONUT OIL; COD LIVER OIL; GLYCERYL MONOOLEATE; MINERAL OIL; PARAFFIN; PROPYLENE GLYCOL; SORBITOL; WATER

Drug Facts

Active Ingredient

Dimethicone, 1%

Zinc Oxide, 10%

Purpose

Skin Protectant

Skin Protectant

Uses

- Helps treat and prevent diaper rash
- Protects chafed skin due to diaper rash and helps seal out wetness

Warnings

For external use only

When using this product

- do not get into eyes

Stop use and ask a doctor if

- condition worsens
- symptoms last more than 7 days or clear up and occur again within a few days

Keep out of reach of children.

If swallowed, get medical help or contact a Poison Control Center right away.

Directions

- use after each diaper change.
- apply cream liberally to keep moisture away during night time or extended exposure to wetness.
- use as needed.

Inactive ingredients

Inactive Ingredients: Aloe Barbadensis Leaf Juice, Beeswax, Benzyl Alcohol, Caprylic/Capric Triglyceride, Ceresin Wax (Ozokerite), Cocos Nucifera (Coconut) Oil, Cod Liver Oil (contains Vitamins A & D), Fragrance, Glyceryl Monooleate, Mineral Oil, Paraffin, Propylene Glycol, Sorbitol, Water (purified)

Other information

Store between 20°-25°C (68°-77°F)

Questions ?

1800-222-1087

Principal Display panel -Tube

CVS Diaper Rash Cream with A&D NDC 51316-625-40

Dimethicone 1% Skin Protectant

Zinc Oxide 10% Skin Protectant

NET WT 4.0 oz (113g)

Principal Display Panel -Carton

CVS Diaper Rash Cream with A&D NDC 51316-625-40

Dimethicone 1% Skin Protectant

Zinc Oxide 10% Skin Protectant

NET WT 4.0 oz (113g)